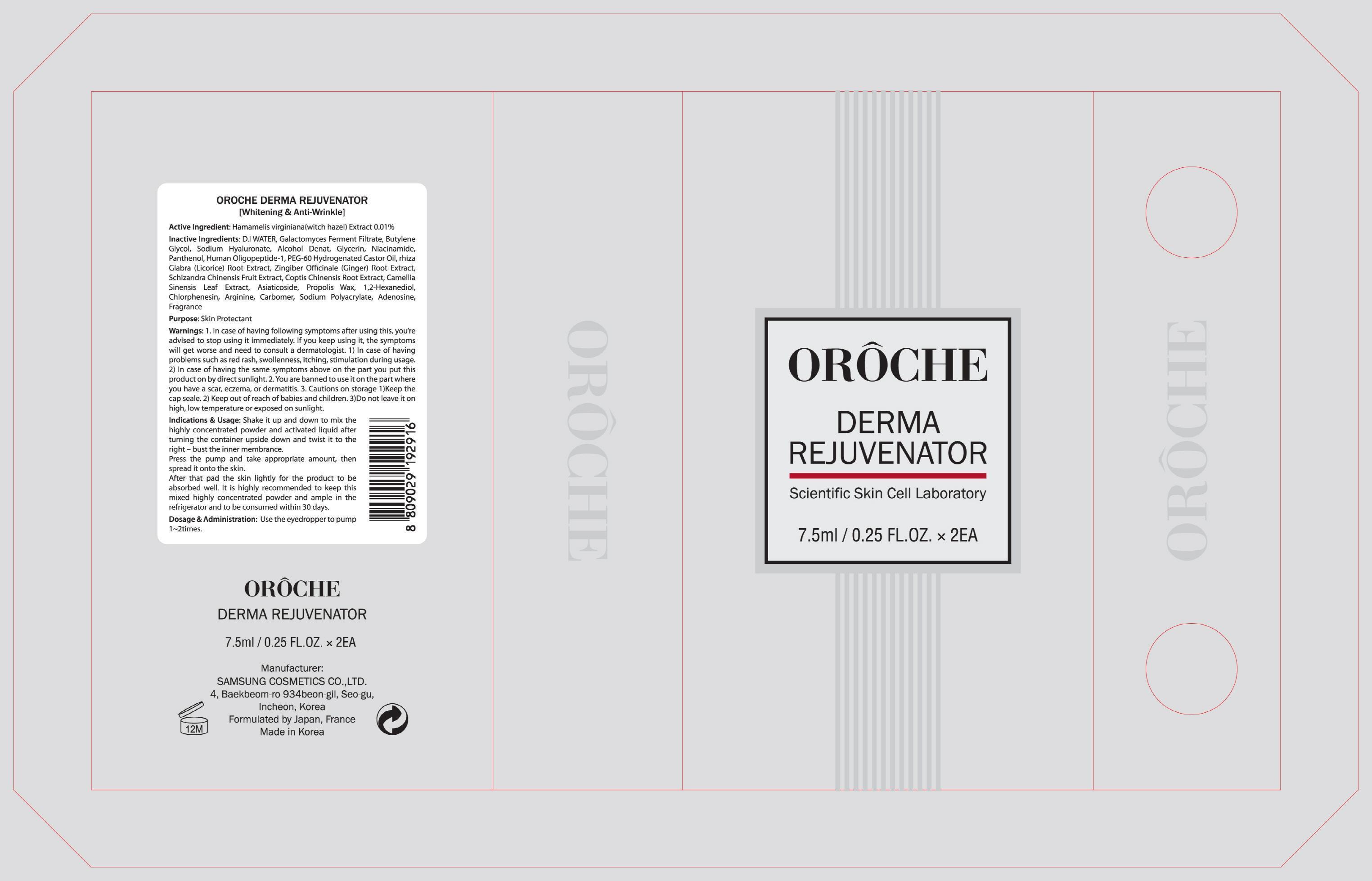 DRUG LABEL: OROCHE DERMA REJUVENATOR
NDC: 69712-010 | Form: CREAM
Manufacturer: OROCHE
Category: otc | Type: HUMAN OTC DRUG LABEL
Date: 20150407

ACTIVE INGREDIENTS: Witch Hazel 0.001 mg/12 mL
INACTIVE INGREDIENTS: WATER; Butylene Glycol

ACTIVE INGREDIENT

Active Ingredient: Hamamelis virginiana(Witch Hazel) Extract 0.01%

INACTIVE INGREDIENT

Inactive Ingredients: D.I WATER, Galactomyces Ferment Filtrate, Butylene Glycol, Sodium Hyaluronate, Alcohol Denat., Glycerin, Niacinamide, Panthenol, Human Oligopeptide-1, PEG-60 Hydrogenated Castor Oil, rhiza Glabra (Licorice) Root Extract, Zingiber Officinale (Ginger) Root Extract, Schizandra Chinensis Fruit Extract, Coptis Chinensis Root Extract, Camellia Sinensis Leaf Extract, Asiaticoside, Propolis Wax, 1,2-Hexanediol, Chlorphenesin, Arginine, Carbomer, Sodium Polyacrylate, Adenosine, Fragrance

PURPOSE

Purpose: Skin Protectant

WARNINGS

Warnings: 1. In case of having following symptoms after using this, you’re advised to stop using it immediately. If you keep using it, the symptoms will get worse and need to consult a dermatologist. 1) In case of having problems such as red rash, swollenness, itching, stimulation during usage. 2) In case of having the same symptoms above on the part you put this product on by direct sunlight. 2. You are banned to use it on the part where you have a scar, eczema, or dermatitis. 3. Cautions on storage 1)Keep the cap seal. 2) Keep out of reach of babies and children 3)Do not leave it on high, low temperature or exposed on sunlight.

KEEP OUT OF REACH OF CHILDREN

Keep out of reach of babies and children

INDICATIONS & USAGE

Indications & Usage: Shake it up and down to mix the highly concentrated powder and activated liquid after turning the container upside down and twist it to the right - bust the inner membrance. Press the pump and take appropriate amount, then spread it onto the skin. After that pad the skin lightly for the product to be absorbed well. It is highly recommended to keep this mixed highly concentrated powder and ample in the refrigerator and to be consumed within 30 days.

DOSAGE & ADMINISTRATION

Dosage & Administration: Use the eyedropper to pump 1-2times.